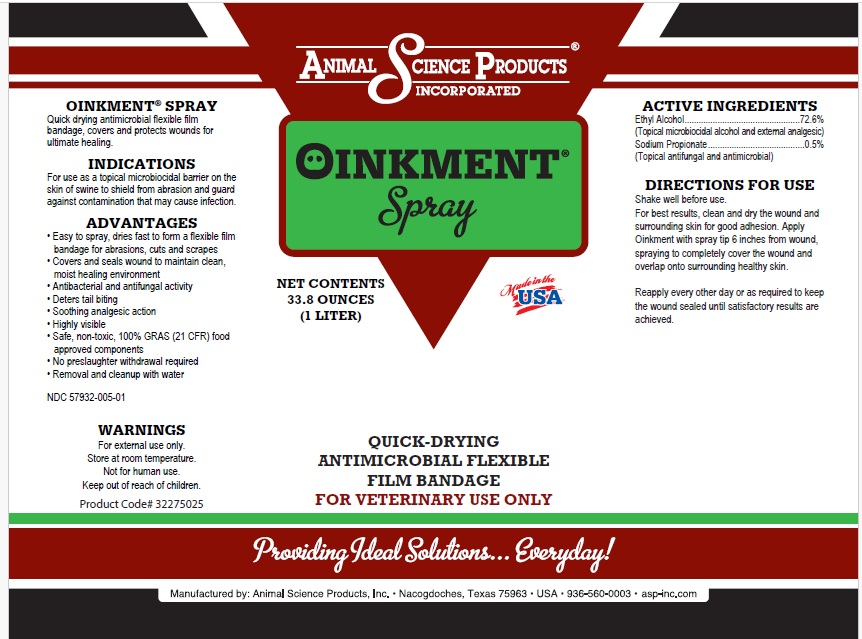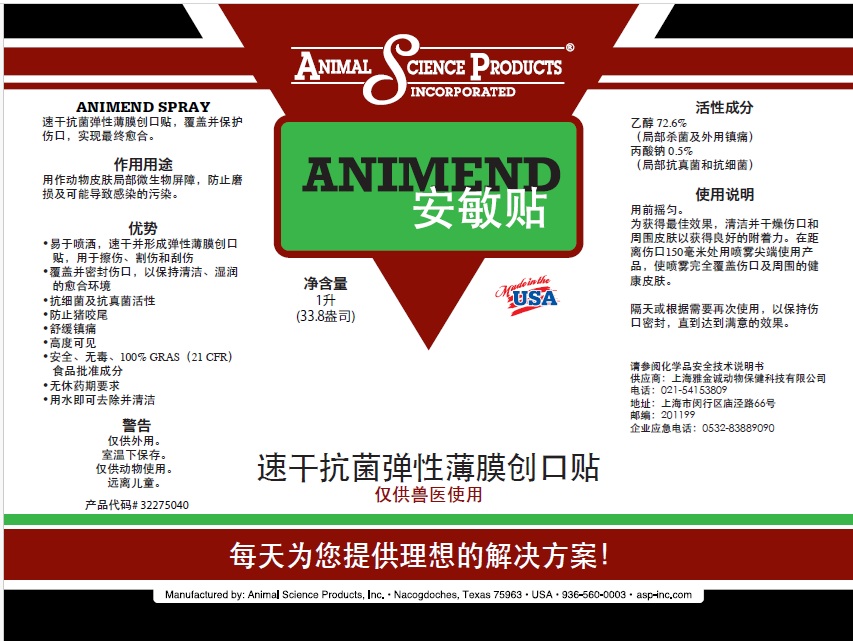 DRUG LABEL: Animal Science Product ANIMEND
NDC: 57932-009 | Form: LIQUID
Manufacturer: Animal Science Products, Inc.
Category: animal | Type: OTC ANIMAL DRUG LABEL
Date: 20250829

ACTIVE INGREDIENTS: ALCOHOL 72.6 g/100 mL; SODIUM PROPIONATE 0.5 g/100 mL
INACTIVE INGREDIENTS: WATER; POWDERED CELLULOSE; FD&C YELLOW NO. 5; FD&C BLUE NO. 1

ANIMEND

Active Ingredient Purpose

Ethyl Alcohol – 72.6% (Topical microbiocidal alcohol and external analgesic)

Sodium Propionate – 0.5% (Topical antifungal and antimicrobial)

Purpose

ANIMEND® SPRAY
Quick-drying antimicrobial flexible film bandage that covers and protects wounds for ultimate healing.

Uses

For use as a topical microbiocidal barrier on the skin of swine to:

- Shield from abrasion
- Guard against contamination that may cause infection

Warnings

- For external use only.
- Store at room temperature.
- Not for human use.
- Keep out of reach of children.

Directions

Shake well before use. For best results, clean and dry the wound and surrounding skin for good adhesion. Apply ANIMEND with spray tip 6 inches from wound, spraying to completely cover the wound and overlap onto surrounding healthy skin.

Reapply every other day or as required to keep the wound sealed until satisfactory results are achieved.

ADVANTAGES

• Easy to spray, dries fast to form a flexible film bandage for abrasions, cuts and scrapes
• Covers and seals wound to maintain clean, moist healing environment
• Antibacterial and antifungal activity
• Deters tail biting
• Soothing analgesic action
• Highly visible
• Safe, non-toxic, 100% GRAS (21 CFR) food approved components
• No preslaughter withdrawal required
• Removal and cleanup with water

Inactive Ingredient

Water, Powdered Cellulose, FD&C Blue #1, FD&C Yellow #5